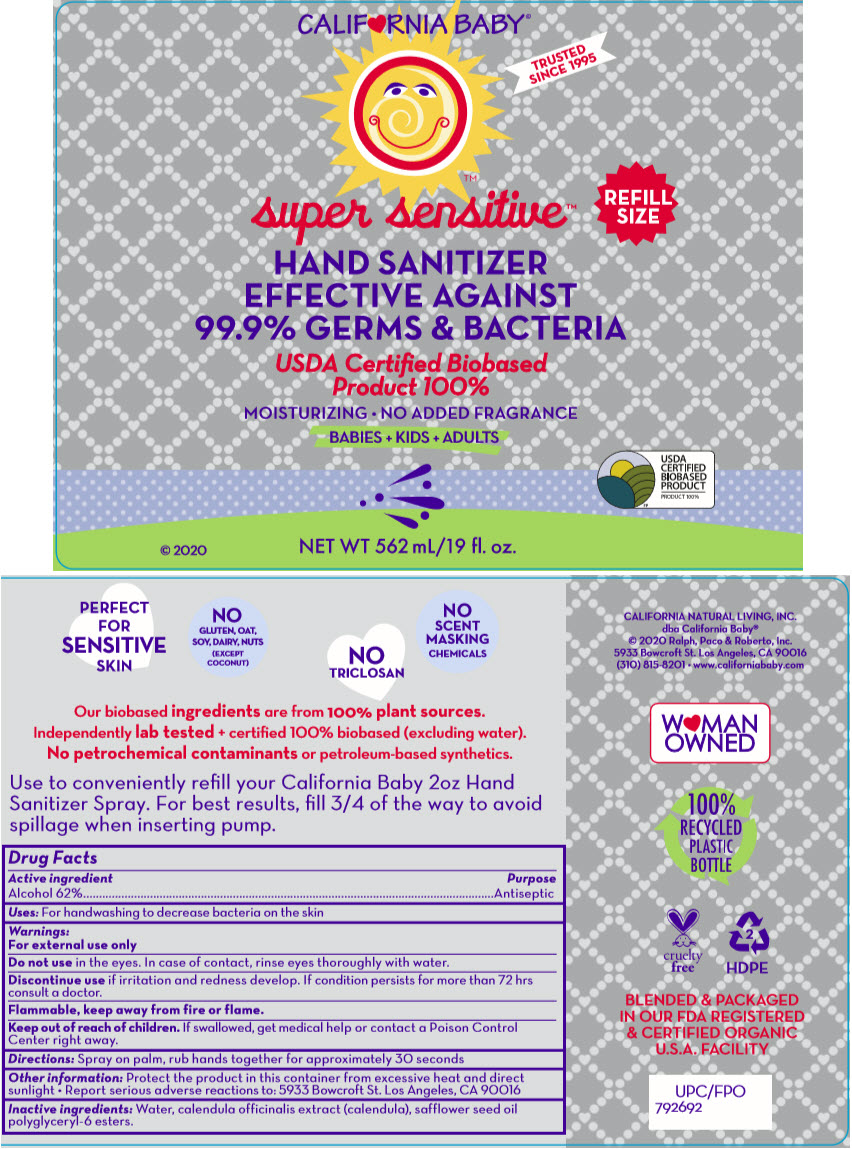 DRUG LABEL: SUPER SENSITIVE HAND SANITIZER
NDC: 52915-076 | Form: SPRAY
Manufacturer: ORGANIC & SUSTAINABLE BEAUTY
Category: otc | Type: HUMAN OTC DRUG LABEL
Date: 20241108

ACTIVE INGREDIENTS: ALCOHOL 62 mL/1 mL
INACTIVE INGREDIENTS: WATER; CALENDULA OFFICINALIS FLOWER

SUPER SENSITIVE™ HAND SANITIZER

Drug Facts

Active ingredient

Alcohol 62%

Purpose

Antiseptic

Uses

For handwashing to decrease bacteria on the skin

Warnings

For external use only

Do not use in the eyes. In case of contact, rinse eyes thoroughly with water.

Discontinue use if irritation and redness develop. If condition persists for more than 72 hrs consult a doctor.

Flammable, keep away from fire or flame.

Keep out of reach of children. If swallowed, get medical help or contact a Poison Control Center right away.

Directions

Spray on palm, rub hands together for approximately 30 seconds

Other information

Protect the product in this container from excessive heat and direct sunlight

- Report serious adverse reactions to: 5933 Bowcroft St. Los Angeles, CA 90016

Inactive ingredients

Water, calendula officinalis extract (calendula), safflower seed oil polyglyceryl-6 esters.

PRINCIPAL DISPLAY PANEL - 562 mL Bottle Label

CALIF♥RNIA BABY®

TRUSTED
SINCE 1995

super sensitive™

REFILL
SIZE

HAND SANITIZER
EFFECTIVE AGAINST
99.9% GERMS & BACTERIA

USDA Certiﬁed Biobased
Product 100%

MOISTURIZING • NO ADDED FRAGRANCE

BABIES + KIDS + ADULTS

© 2020

NET WT 562 mL/19 fl. oz.

USDA
CERTIFIED
BIOBASED
PRODUCT
PRODUCT 100%